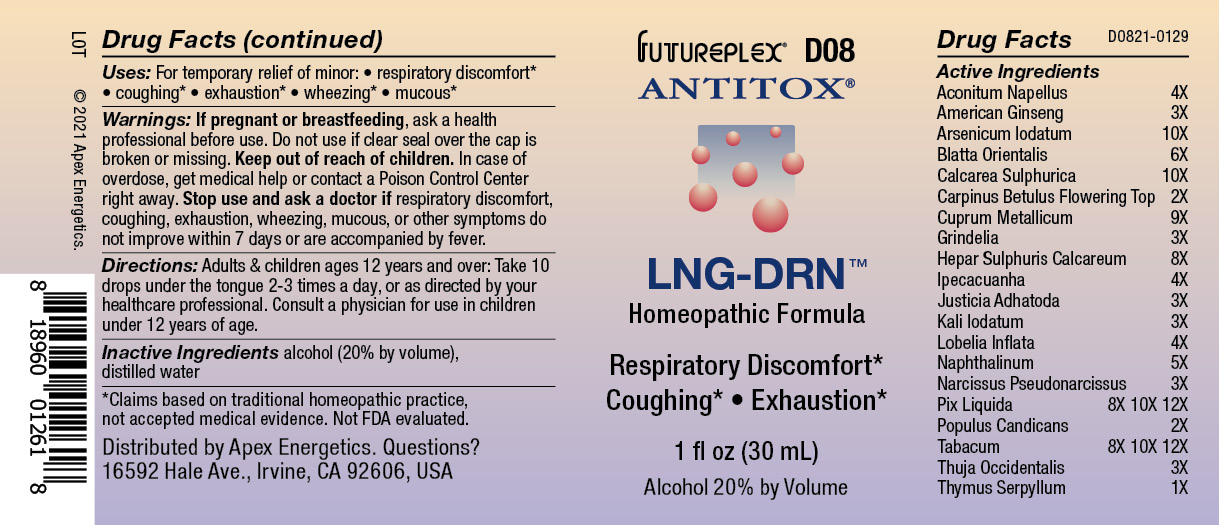 DRUG LABEL: D08
NDC: 63479-0408 | Form: SOLUTION/ DROPS
Manufacturer: Apex Energetics Inc.
Category: homeopathic | Type: HUMAN OTC DRUG LABEL
Date: 20240108

ACTIVE INGREDIENTS: ACONITUM NAPELLUS 4 [hp_X]/1 mL; CALCIUM SULFATE ANHYDROUS 10 [hp_X]/1 mL; CARPINUS BETULUS FLOWERING TOP 2 [hp_X]/1 mL; LOBELIA INFLATA 4 [hp_X]/1 mL; BLATTA ORIENTALIS 6 [hp_X]/1 mL; JUSTICIA ADHATODA LEAF 3 [hp_X]/1 mL; POTASSIUM IODIDE 3 [hp_X]/1 mL; PINE TAR 12 [hp_X]/1 mL; ARSENIC TRIIODIDE 10 [hp_X]/1 mL; CALCIUM SULFIDE 8 [hp_X]/1 mL; NAPHTHALENE 5 [hp_X]/1 mL; NARCISSUS PSEUDONARCISSUS 3 [hp_X]/1 mL; TOBACCO LEAF 12 [hp_X]/1 mL; THUJA OCCIDENTALIS LEAFY TWIG 3 [hp_X]/1 mL; AMERICAN GINSENG 3 [hp_X]/1 mL; POPULUS BALSAMIFERA LEAF BUD 2 [hp_X]/1 mL; THYMUS SERPYLLUM 1 [hp_X]/1 mL; IPECAC 4 [hp_X]/1 mL; COPPER 9 [hp_X]/1 mL; GRINDELIA HIRSUTULA FLOWERING TOP 3 [hp_X]/1 mL
INACTIVE INGREDIENTS: ALCOHOL; WATER

D08

Active Ingredients
Aconitum Napellus | 4X
American Ginseng | 3X
Arsenicum Iodatum | 10X
Blatta Orientalis | 6X
Calcarea Sulphurica | 10X
Carpinus Betulus Flowering Top | 2X
Cuprum Metallicum | 9X
Grindelia | 3X
Hepar Sulphuris Calcareum | 8X
Ipecacuanha | 4X
Justicia Adhatoda | 3X
Kali Iodatum | 3X
Lobelia Inflata | 4X
Naphthalinum | 5X
Narcissus Pseudonarcissus | 3X
Pix Liquida | 8X 10X 12X
Populus Candicans | 2X
Tabacum | 8X 10X 12X
Thuja Occidentalis | 3X
Thymus Serpyllum | 1X

INDICATIONS AND USAGE

Uses:

For temporary relief of minor:

respiratory discomfort*

coughing*

exhaustion*

wheezing*

mucous*

*Claims based on traditional homeopathic practice, not accepted medical evidence. Not FDA evaluated.

Warnings:

PREGNANCY OR BREAST FEEDING

If pregnant or breastfeeding, ask a health professional before use.

Do not use if clear seal over the cap is broken or missing.

Keep out of reach of children. In case of overdose, get medical help or contact a Poison Control Center right away.

Stop use and ask a doctor if respiratory discomfort, coughing, exhaustion, wheezing, mucous, or other symptoms do not improve within 7 days or are accompanied by fever.

Directions:

Adults & children ages 12 years and over: Take 10 drops under the tongue 2-3 times a day, or as directed by your healthcare professional. Consult a physician for use in children under 12 years of age.

Inactive Ingredients

alcohol (20% by volume), distilled water

Distributed by Apex Energetics. Questions?

16592 Hale Ave., Irvine, CA 92606, USA

PACKAGE LABEL

FUTUREPLEX® D08

ANTITOX®

LNG-DRN™

Homeopathic Formula

Respiratory Discomfort*

Coughing* Exhaustion*

1 fl oz (30 mL)

Alcohol 20% by Volume